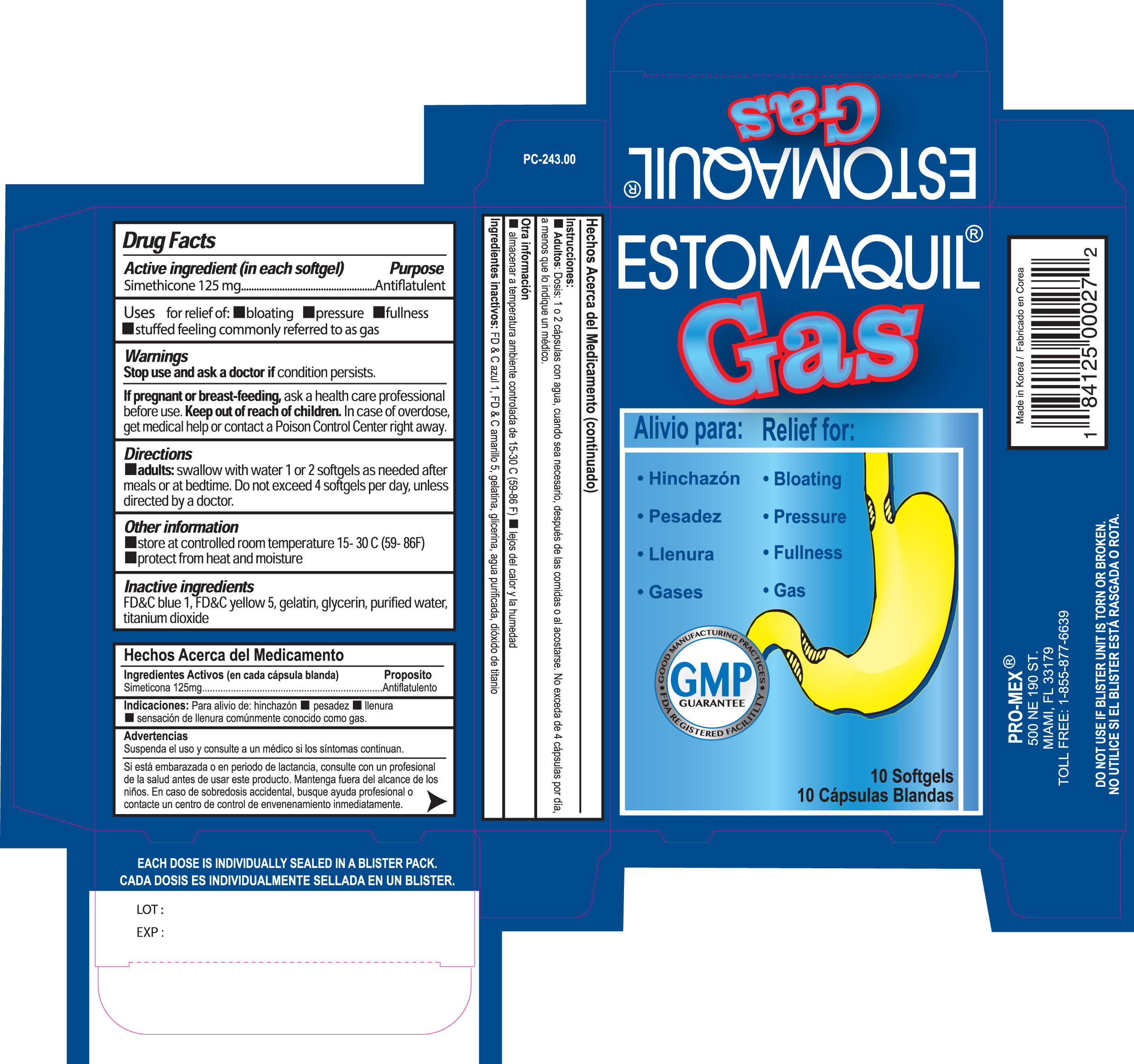 DRUG LABEL: Estomaquil Gas Relief
NDC: 58988-1800 | Form: CAPSULE, LIQUID FILLED
Manufacturer: Promex LLC
Category: otc | Type: HUMAN OTC DRUG LABEL
Date: 20150109

ACTIVE INGREDIENTS: DIMETHICONE 125 mg/1 1
INACTIVE INGREDIENTS: FD&C BLUE NO. 1; FD&C YELLOW NO. 5; GELATIN; GLYCERIN; WATER; TITANIUM DIOXIDE

Drug Facts

Active Ingredients (in each softgel)

Simethicone 125mg

Purpose

Antiflatulent

Uses

For Relief of:

- Bloating
- Pressure
- Fullness
- stuffed feeling commonly referred to as gas

Warnings

Stop use and ask a doctor if

condition persists

If pregnant or breast-feeding,

ask a health care professional before use.

Keep out of reach of children

In case of overdose, get medical help or contact a Poison Control Center right away.

Directions

- adults: swallow with water 1 or 2 softgels as needed after meals or at bedtime. Do not exceed 4 softgels per day, unless directed by doctor.

Other information

- store at a controlled room temperature 15-30°C (59-86°F)
- protect from heat and moisture

Inactive ingreients

FD&C blue 1, FD&C yellow 5, gelatin, glycerin, purified water, titanium dioxide